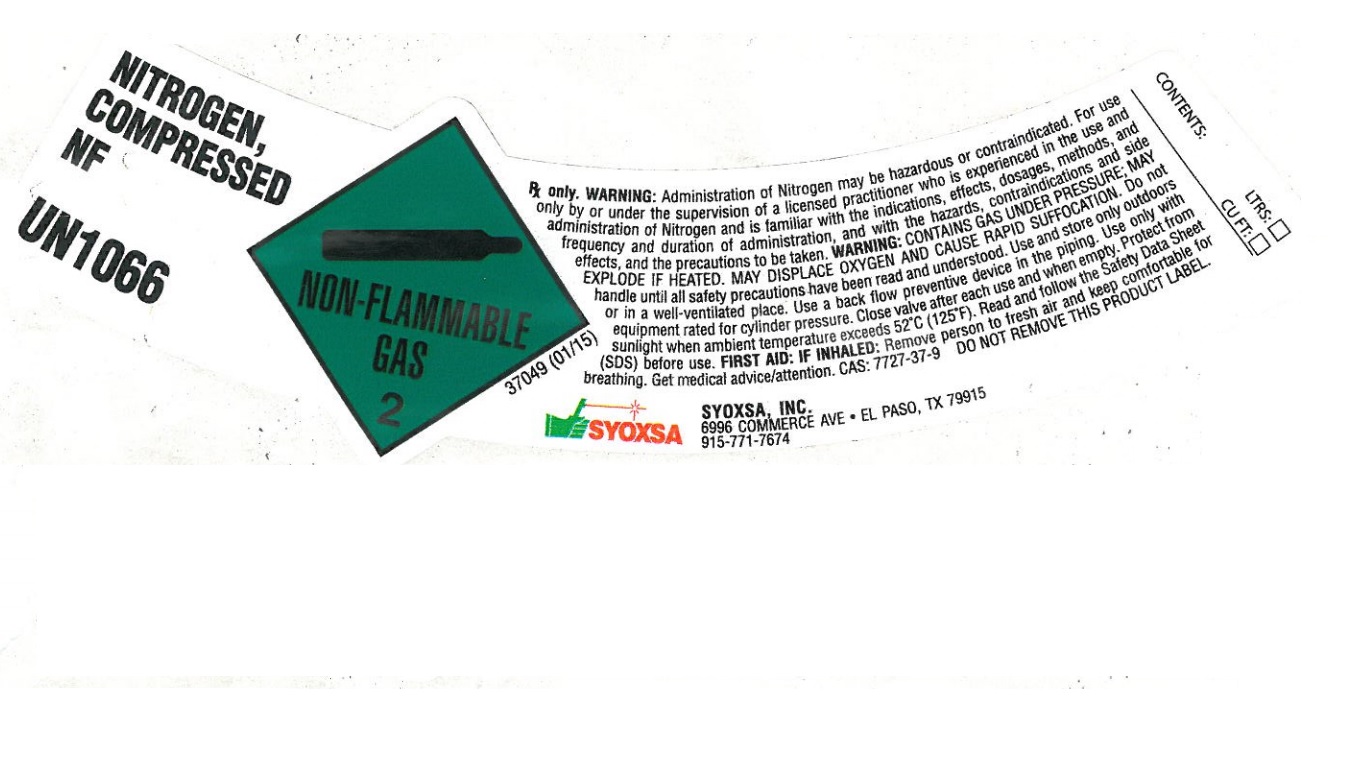 DRUG LABEL: Nitrogen
NDC: 23647-002 | Form: GAS
Manufacturer: SYOXSA, Inc.
Category: prescription | Type: HUMAN PRESCRIPTION DRUG LABEL
Date: 20251212

ACTIVE INGREDIENTS: NITROGEN 990 mL/1 L

nitrogen

PACKAGE LABEL

NITROGEN, COMPRESSED NF
UN1066
RX only. WARNING: Administration of Nitrogen may be hazardous or contraindicated. For use only by or under the supervision of a licensed practitioner who is experienced in the use and administration of Nitrogen and is familiar with the indications, effects, dosages, methods, and frequency and duration of administration, and with the hazards, contraindications and side effects, and the precautions to be taken. WARNING: CONTAINS GAS UNDER PRESSURE; MAY EXPLODE IF HEATED. MAY DISPLACE OXYGEN AND CAUSE RAPID SUFFOCATION. Do not handle until all safety precautions have been read and understood. Use and store only outdoor or in a well-ventilated place. Use a back flow preventive device in the piping. Use only with equipment rated for cylinder pressure. Close valve after each use and when empty. Protect from sunlight when ambient temperature exceeds 52 degrees C (125 degrees F). Read and follow the Safety Date Sheet (SDS) before use. FIRST AID: IF INHALED: Remove person to fresh air and keep comfortable for breathing. Get medical advice/attention. CAS 7727-37-9 DO NOT REMOVE THIS PRODUCT LABEL.
SYOXSA
SYOXSA, INC.
6996 COMMERCE AVE. EL PASO, TX 79915
915-771-7674